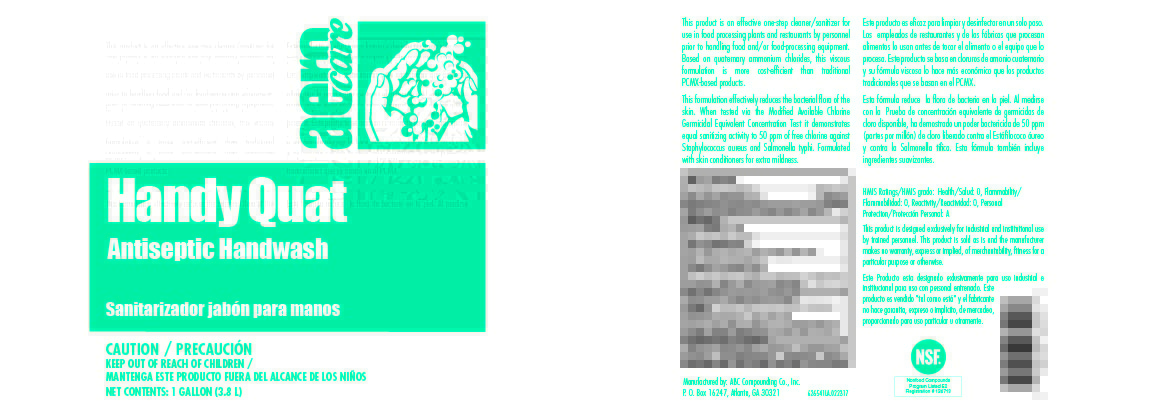 DRUG LABEL: Aero Care Handy Quat Antiseptic Handwash
NDC: 62257-265 | Form: SOAP
Manufacturer: ABC Compounding Co., Inc.
Category: otc | Type: HUMAN OTC DRUG LABEL
Date: 20251119

ACTIVE INGREDIENTS: BENZALKONIUM CHLORIDE 25 mg/1 mL
INACTIVE INGREDIENTS: ISOPROPYL ALCOHOL; HYDROXYETHYL CELLULOSE (1500 MPA.S AT 1%); DISODIUM COCOAMPHODIPROPIONATE; LAURAMINE OXIDE; PEG-75 LANOLIN; GLYCERIN; CITRIC ACID MONOHYDRATE; FD&C RED NO. 4; WATER

Aero Care Handy Quat Antiseptic Handwash 6265 Drug facts and Label

Drug Facts Box OTC-Active Ingredient Section

Benzalkonium Chloride 2.5%

Drug Facts Box OTC-Purpose Section

Antiseptic

Drug Facts Box OTC-Indications & Usage Section

for hand-washing to decrease bacteria on the skin

Drug Facts Box OTC-Warnings Section

For external use only

Drug Facts Box OTC-When Using Section

do not get into eyes

if contact occurs, rinse eyes thoroughly with water

Drug Facts Box OTC-Stop Use Section

irritation and redness develop

Drug Facts Box OTC-Keep Out of Reach of Children Section

if swallowed, get medical help or contact a Poison Control Center right away

Drug Facts Box OTC-Dosage & Administration Section

- wet hands and forearms
- apply 5 milliliters (teaspoonful) or palmful to hands and forearms
- scrub thoroughly for 1 minute and rinse

Drug Facts Box OTC-Inactive Ingredients Section

water, glycerin, isopropyl alcohol, disodium cocoamphodiproprionate, hydroxyethylcellulose, lauramine oxide,

PEG-75 lanolin, citric acid, FD and C red no.4

Handy Quat 6265 1 Gallon Label